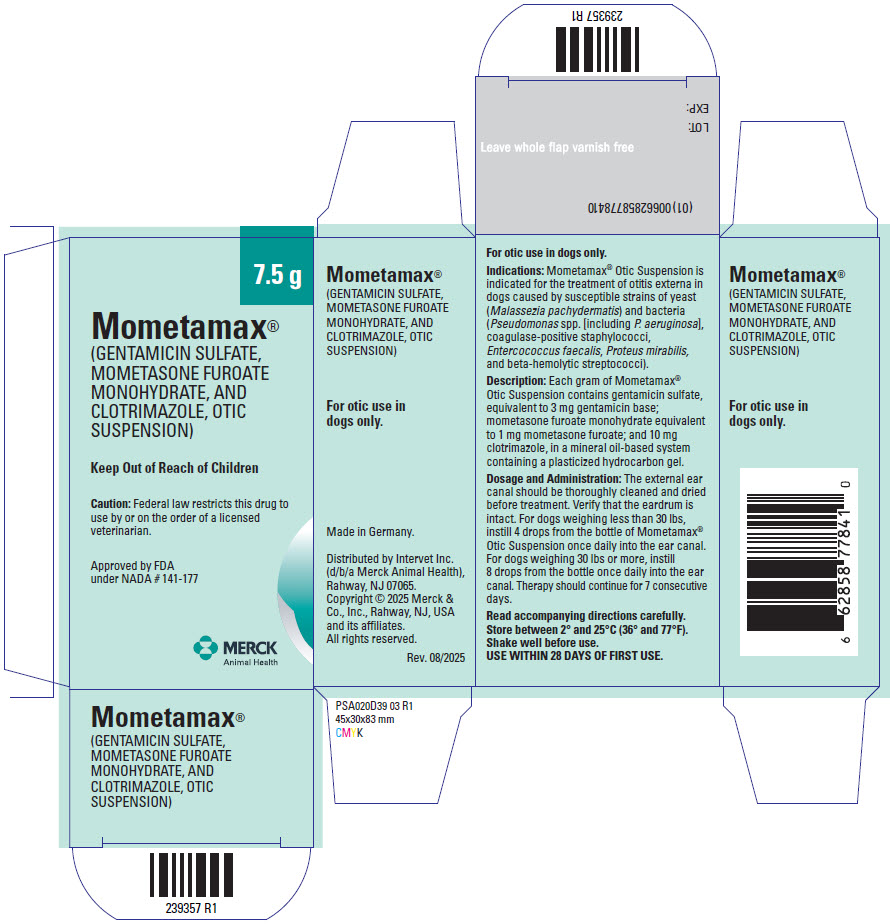 DRUG LABEL: Mometamax
NDC: 0061-1246 | Form: SUSPENSION
Manufacturer: Merck Sharp & Dohme Corp.
Category: animal | Type: PRESCRIPTION ANIMAL DRUG LABEL
Date: 20251208

ACTIVE INGREDIENTS: GENTAMICIN SULFATE 3 mg/1 g; MOMETASONE FUROATE MONOHYDRATE 1 mg/1 g; CLOTRIMAZOLE 10 mg/1 g

MOMETAMAX®
(GENTAMICIN SULFATE,
MOMETASONE FUROATE
MONOHYDRATE, AND
CLOTRIMAZOLE,
OTIC SUSPENSION)

Approved by FDA under
NADA # 141-177

239358 R5
PRODUCT
INFORMATION

VETERINARY

For Otic Use in Dogs Only

SAFE HANDLING WARNING

CAUTION: Federal law restricts this drug to use by or on the order of a licensed veterinarian.

Keep this and all drugs out of the reach of children.

DESCRIPTION

DESCRIPTION: Each gram of MOMETAMAX Otic Suspension contains gentamicin sulfate, equivalent to 3 mg gentamicin base; mometasone furoate monohydrate equivalent to 1 mg mometasone furoate; and 10 mg clotrimazole, in a mineral oil-based system containing a plasticized hydrocarbon gel.

CLINICAL PHARMACOLOGY

PHARMACOLOGY:

Gentamicin: Gentamicin sulfate is an aminoglycoside antibiotic active against a wide variety of gram-negative and gram-positive bacteria. In vitro tests have determined that gentamicin is bactericidal and acts by inhibiting normal protein synthesis in susceptible microorganisms. In clinical trials, gentamicin was shown to have a range of activity against the following organisms commonly isolated from infected canine ears: Pseudomonas spp. (including P. aeruginosa), coagulase-positive staphylococci, Enterococcus faecalis, Proteus mirabilis, and beta-hemolytic streptococci.

Mometasone: Mometasone furoate monohydrate is a synthetic adrenocorticoid characterized by a novel (2) furoate 17-ester having chlorine at the 9 and 21 positions, which have shown to possess high topical potency.

Systemic absorption of mometasone furoate ointment was found to be minimal (2%) over 1 week when applied topically to dogs with intact skin. In a 6-month dermal toxicity study using 0.1% mometasone ointment on healthy intact skin in dogs, systemic effects typical of corticosteroid therapy were noted.

The extent of percutaneous absorption of topical corticosteroids is determined by many factors including the integrity of the epidermal barrier. Topical corticosteroids can be absorbed from normal, intact skin. Inflammation can increase percutaneous absorption. Once absorbed through the skin, topical corticosteroids are handled through pharmacokinetic pathways similar to systemically administered corticosteroids.

Clotrimazole: Clotrimazole is a broad-spectrum antifungal agent that is used for the treatment of dermal infections caused by various species of dermatophytes and yeast. The primary action of clotrimazole is against dividing and growing organisms.

In vitro, clotrimazole exhibits fungistatic and fungicidal activity against isolates of Trichophyton rubrum, Trichophyton mentagrophytes, Epidermophyton floccosum, Microsporum canis, Candida spp., and Malassezia pachydermatis. Resistance to clotrimazole is very rare among the fungi that cause superficial mycoses. In an induced otitis externa study using dogs infected with Malassezia pachydermatis, 1% clotrimazole in the vehicle formulation was effective both microbiologically and clinically in terms of reduction of exudate, odor, and swelling.

In studies of the mechanism of action, the minimum fungicidal concentration of clotrimazole caused leakage of intracellular phosphorus compounds into the ambient medium with concomitant breakdown of cellular nucleic acids and accelerated potassium efflux. These events began rapidly and extensively after addition of the drug. Clotrimazole is very poorly absorbed following dermal application.

Gentamicin-Mometasone-Clotrimazole: By virtue of its three active ingredients, MOMETAMAX Otic Suspension has antibacterial, anti-inflammatory, and antifungal activity. In clinical field trials, MOMETAMAX Otic Suspension was effective in the treatment of otitis externa associated with bacteria and Malassezia pachydermatis. MOMETAMAX Otic Suspension reduced discomfort, redness, swelling, exudate, and odor.

VETERINARY INDICATIONS

INDICATIONS: MOMETAMAX Otic Suspension is indicated for the treatment of otitis externa in dogs caused by susceptible strains of yeast (Malassezia pachydermatis) and bacteria (Pseudomonas spp. [including P. aeruginosa], coagulase-positive staphylococci, Enterococcus faecalis, Proteus mirabilis, and beta-hemolytic streptococci).

CONTRAINDICATIONS

CONTRAINDICATIONS: If hypersensitivity to any of the components occurs, treatment should be discontinued and appropriate therapy instituted. Concomitant use of drugs known to induce ototoxicity should be avoided. Do not use in dogs with known perforation of eardrums.

WARNINGS

WARNINGS: The use of these components has been associated with deafness or partial hearing loss in a small number of sensitive dogs (e.g., geriatric). The hearing deficit is usually temporary. If hearing or vestibular dysfunction is noted during the course of treatment, discontinue use of MOMETAMAX Otic Suspension immediately and flush the ear canal thoroughly with a non-ototoxic solution.

Corticosteroids administered to dogs, rabbits, and rodents during pregnancy have resulted in cleft palate in offspring. Other congenital anomalies including deformed forelegs, phocomelia, and anasarca have been reported in offspring of dogs that received corticosteroids during pregnancy.

Field and experimental data have demonstrated that corticosteroids administered orally or parenterally to animals may induce the first stage of parturition if used during the last trimester of pregnancy and may precipitate premature parturition followed by dystocia, fetal death, retained placenta, and metritis.

PRECAUTIONS

PRECAUTIONS: Before instilling any medication into the ear, examine the external ear canal thoroughly to be certain the tympanic membrane is not ruptured in order to avoid the possibility of transmitting infection to the middle ear as well as damaging the cochlea or vestibular apparatus from prolonged contact.

Administration of recommended doses of MOMETAMAX Otic Suspension beyond 7 days may result in delayed wound healing.

If overgrowth of nonsusceptible bacteria or fungi occurs, treatment should be discontinued and appropriate therapy instituted.

Avoid ingestion. Adverse systemic reactions have been observed following the oral ingestion of some topical corticosteroid preparations. Patients should be closely observed for the usual signs of adrenocorticoid overdosage which include sodium retention, potassium loss, fluid retention, weight gain, polydipsia, and/or polyuria. Prolonged use or overdosage may produce adverse immunosuppressive effects.

Use of corticosteroids, depending on dose, duration, and specific steroid, may result in endogenous steroid production inhibition following drug withdrawal. In patients presently receiving or recently withdrawn from corticosteroid treatments, therapy with a rapidly acting corticosteroid should be considered in especially stressful situations.

ANIMAL PHARMACOLOGY AND OR TOXICOLOGY

TOXICOLOGY: Field and safety studies with MOMETAMAX Otic Suspension have shown a wide safety margin at the recommended dose level in dogs (see PRECAUTIONS/ADVERSE REACTIONS).

ADVERSE REACTIONS

ADVERSE REACTIONS:

Gentamicin: While aminoglycosides are absorbed poorly from skin, intoxication may occur when aminoglycosides are applied topically for prolonged periods of time to large wounds, burns, or any denuded skin, particularly if there is renal insufficiency. All aminoglycosides have the potential to produce reversible and irreversible vestibular, cochlear, and renal toxicity.

Mometasone: ALP (SAP) and ALT (SGPT) enzyme elevations, weight loss, anorexia, polydipsia, polyuria, neutrophilia, and lymphopenia have occurred following the use of parenteral, high-dose, and/or prolonged or systemic synthetic corticosteroids in dogs. Cushing's syndrome in dogs has been reported in association with prolonged or repeated steroid therapy.

Clotrimazole: The following have been reported occasionally in humans in connection with the use of clotrimazole: erythema, stinging, blistering, peeling, edema, pruritus, urticaria, and general irritation of the skin not present before therapy.

MOMETAMAX Otic Suspension: In field studies following once daily treatment with MOMETAMAX Otic Suspension, ataxia, proprioceptive deficits, and increased water consumption were observed in less than 1% of 164 dogs. In a field study following twice-daily treatment with MOMETAMAX Otic Suspension, inflammation of the pinna and diarrhea were observed in less than 1% of 141 dogs.

DOSAGE AND ADMINISTRATION:

The external ear canal should be thoroughly cleaned and dried before treatment. Verify that the eardrum is intact. For dogs weighing less than 30 lbs, instill 4 drops from the 7.5 g, 15 g, and 30 g bottles (2 drops from the 215 g bottle) of MOMETAMAX Otic Suspension once daily into the ear canal. For dogs weighing 30 lbs or more, instill 8 drops from the 7.5 g, 15 g, and 30 g bottles (4 drops from the 215 g bottle) once daily into the ear canal. Therapy should continue for 7 consecutive days.

HOW SUPPLIED

HOW SUPPLIED: MOMETAMAX Otic Suspension is available in 7.5 g, 15 g, 30 g, and 215 g plastic bottles.

STORAGE AND HANDLING

Store between 2° and 25°C (36° and 77°F). Shake well before use.

USE WITHIN 28 DAYS OF FIRST USE.

Distributed by Intervet Inc. (d/b/a Merck Animal Health),
Rahway, NJ 07065.

Made in Germany.

Copyright © 2025 Merck & Co., Inc., Rahway, NJ, USA and its affiliates.
All rights reserved.

Rev. 11/2025

PRINCIPAL DISPLAY PANEL - 7.5 g Bottle Carton

7.5 g

Mometamax®
(GENTAMICIN SULFATE,
MOMETASONE FUROATE
MONOHYDRATE, AND
CLOTRIMAZOLE, OTIC
SUSPENSION)

Keep Out of Reach of Children

Caution: Federal law restricts this drug to
use by or on the order of a licensed
veterinarian.

Approved by FDA
under NADA # 141-177

MERCK
Animal Health